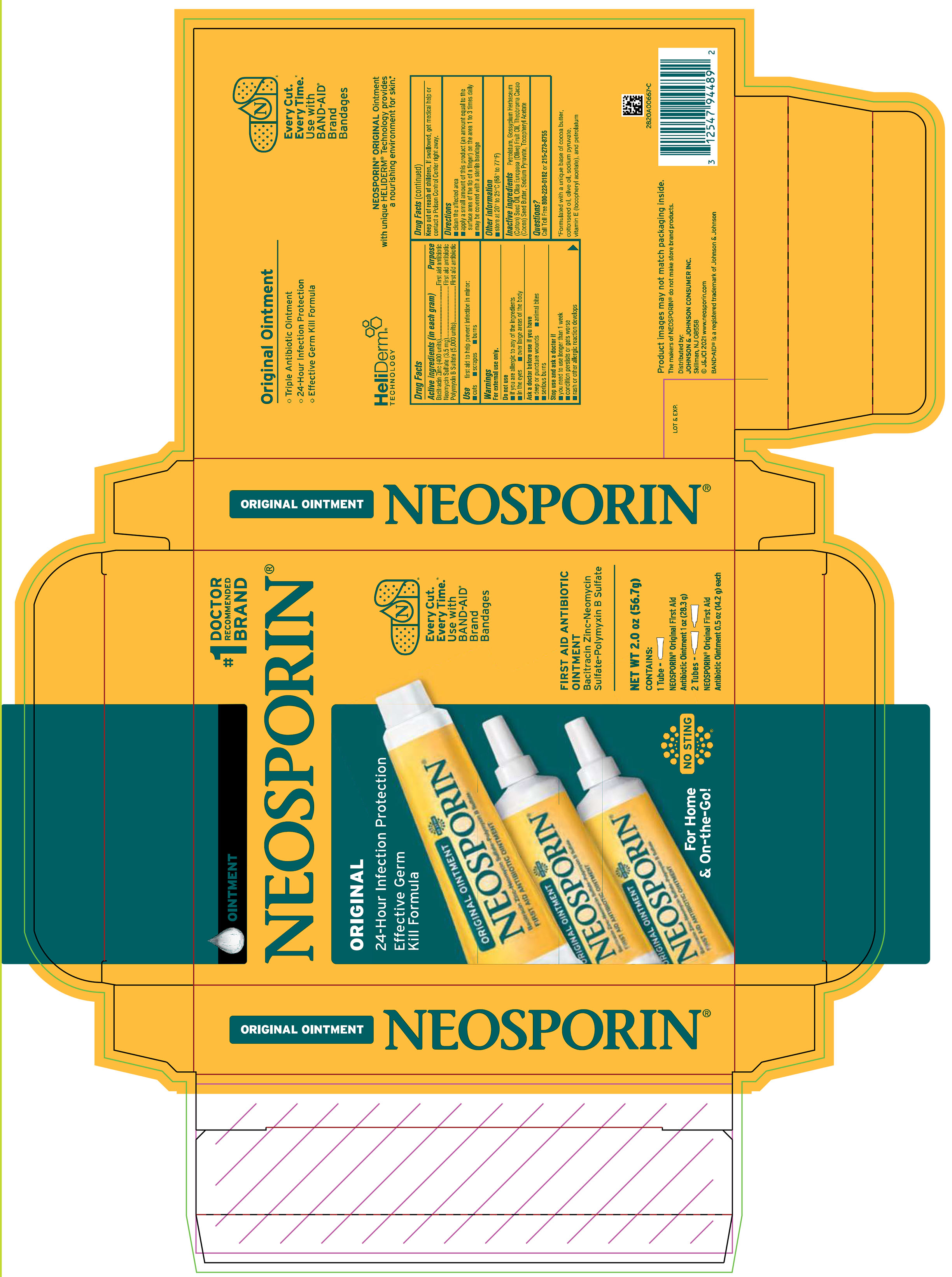 DRUG LABEL: Neosporin Original
NDC: 69968-0843 | Form: KIT | Route: TOPICAL
Manufacturer: Kenvue Brands LLC
Category: otc | Type: HUMAN OTC DRUG LABEL
Date: 20250221

ACTIVE INGREDIENTS: NEOMYCIN SULFATE 3.5 mg/1 g; POLYMYXIN B SULFATE 5000 [iU]/1 g; BACITRACIN ZINC 400 [iU]/1 g; BACITRACIN ZINC 400 [iU]/1 g; NEOMYCIN SULFATE 3.5 mg/1 g; POLYMYXIN B SULFATE 5000 [iU]/1 g
INACTIVE INGREDIENTS: OLIVE OIL; COCOA BUTTER; SODIUM PYRUVATE; ALPHA-TOCOPHEROL ACETATE; PETROLATUM; LEVANT COTTONSEED OIL; OLIVE OIL; LEVANT COTTONSEED OIL; COCOA BUTTER; SODIUM PYRUVATE; ALPHA-TOCOPHEROL ACETATE; PETROLATUM

Neosporin Original Ointment Clubtray

Drug Facts

Active ingredients (in each gram)

Bacitracin Zinc (400 units)

Neomycin Sulfate (3.5 mg)

Polymyxin B sulfate (5,000 units)

Purpose

First aid antibiotic

Use

first aid to help prevent infection in minor:

- cuts
- scrapes
- burns

Warnings

For external use only.

Do not use

- if you are allergic to any of the ingredients
- in the eyes
- over large areas of the body

Ask a doctor before use if you have

- deep or puncture wounds
- animal bites
- serious burns

Stop use and ask a doctor if

- you need to use longer than 1 week
- condition persists or gets worse
- rash or other allergic reaction develops

Keep out of reach of children. If swallowed, get medical help or contact a Poison Control Center right away.

Directions

- clean the affected area
- apply a small amount of this product (an amount equal

to the surface area of the tip of a finger) on the area 1 to 3 times daily

- may be covered with a sterile bandage

Other information

- store at 20° to 25°C (68° to 77° F)

Inactive ingredients

Petrolatum, Gossypium Herbaceum (Cotton) Seed Oil, Olea Europaea (Olive) Fruit Oil, Theobroma Cacao (Cocoa) Seed Butter, Sodium Pyruvate, Tocopheryl Acetate

Questions?

Call Toll Free 800-223-0182 or 215-273-8755

Distributed by:
JOHNSON & JOHNSON CONSUMER INC.
Skillman, NJ 08558

PRINCIPAL DISPLAY PANEL - Kit Package Label

OINTMENT

#1

DOCTOR

RECOMMENDED
BRAND

NEOSPORIN®

ORIGINAL

24-Hour Infection Protection

Effective Germ

Kill Formula

Every Cut.

Every Time.

Use with

BAND-AID

Brand

Bandages

FIRST AID ANTIBIOTIC

OINTMENT

Bacitracin Zinc-Neomycin

Sulfate-Polymyxin B Sulfate

For Home

& On-the-Go!

NO STING

NET WT 2.0 oz (56.7 g)

CONTAINS:

1 Tube –

NEOSPORIN® Original First Aid

Antibiotic Ointment 1 oz (28.3 g)

2 Tubes –

NEOSPORIN® Original First Aid

Antibiotic Ointment 0.5 oz (14.2 g) each